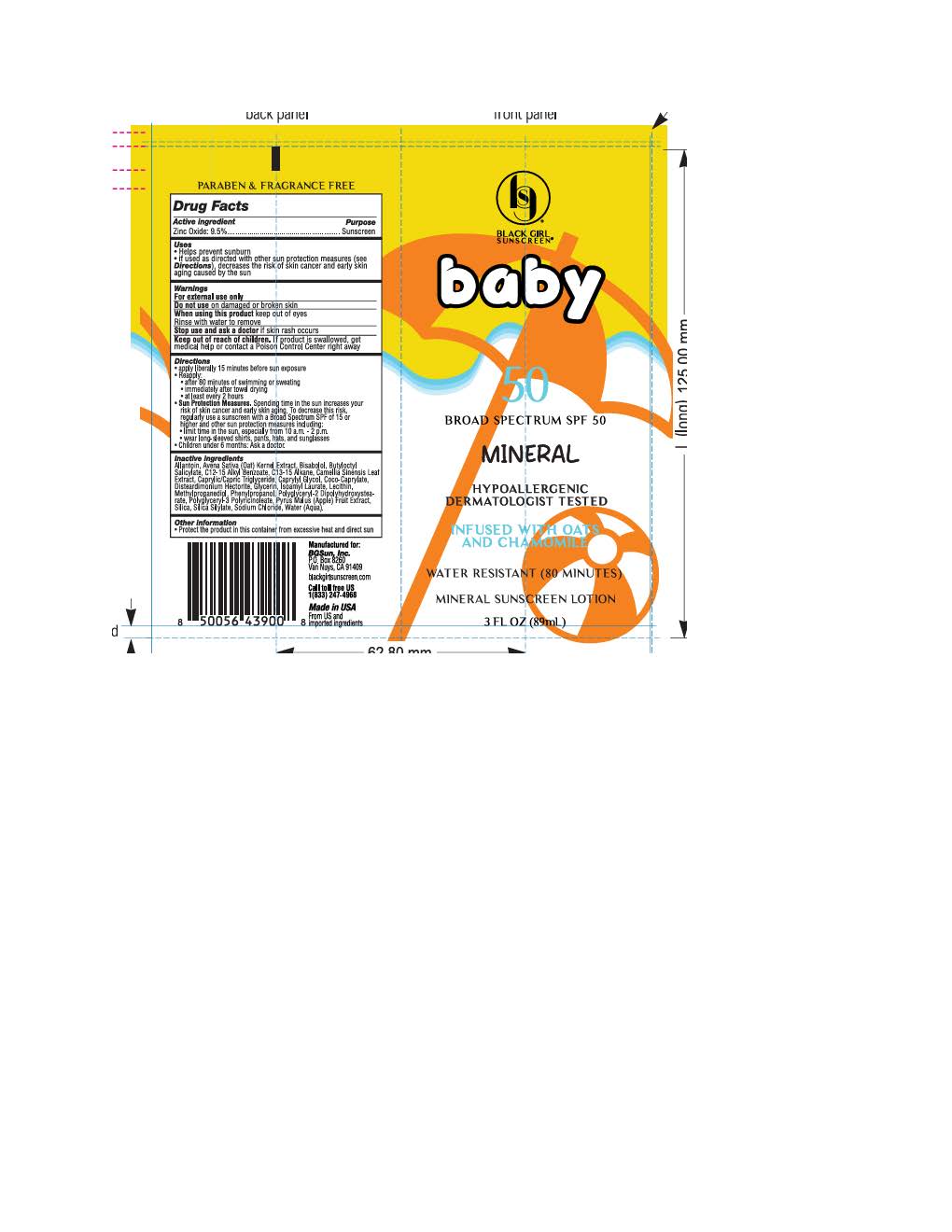 DRUG LABEL: Black Girl Sunscreen Make It Mineral Baby
NDC: 84204-2496 | Form: LOTION
Manufacturer: Black Girl Sunscreen
Category: otc | Type: HUMAN OTC DRUG LABEL
Date: 20251009

ACTIVE INGREDIENTS: ZINC OXIDE 104.5 mg/1 mL
INACTIVE INGREDIENTS: POLYGLYCERYL-2 DIPOLYHYDROXYSTEARATE; ISOAMYL LAURATE; ALKYL (C12-15) BENZOATE; SODIUM CHLORIDE; CAPRYLIC/CAPRIC TRIGLYCERIDE; WATER; COCO-CAPRYLATE; .ALPHA.-BISABOLOL, (+)-; LECITHIN, SOYBEAN; ALLANTOIN; SILICON DIOXIDE; CAPRYLYL GLYCOL; PHENYLPROPANOL; METHYLPROPANEDIOL; GLYCERIN; CAMELLIA SINENSIS LEAF OIL; C13-15 ALKANE; PYRUS MALUS (APPLE) FRUIT; BUTYLOCTYL SALICYLATE; AVENA SATIVA (OAT) KERNEL OIL; DISTEARDIMONIUM HECTORITE

Black Girl Sunscreen Make it Mineral Baby